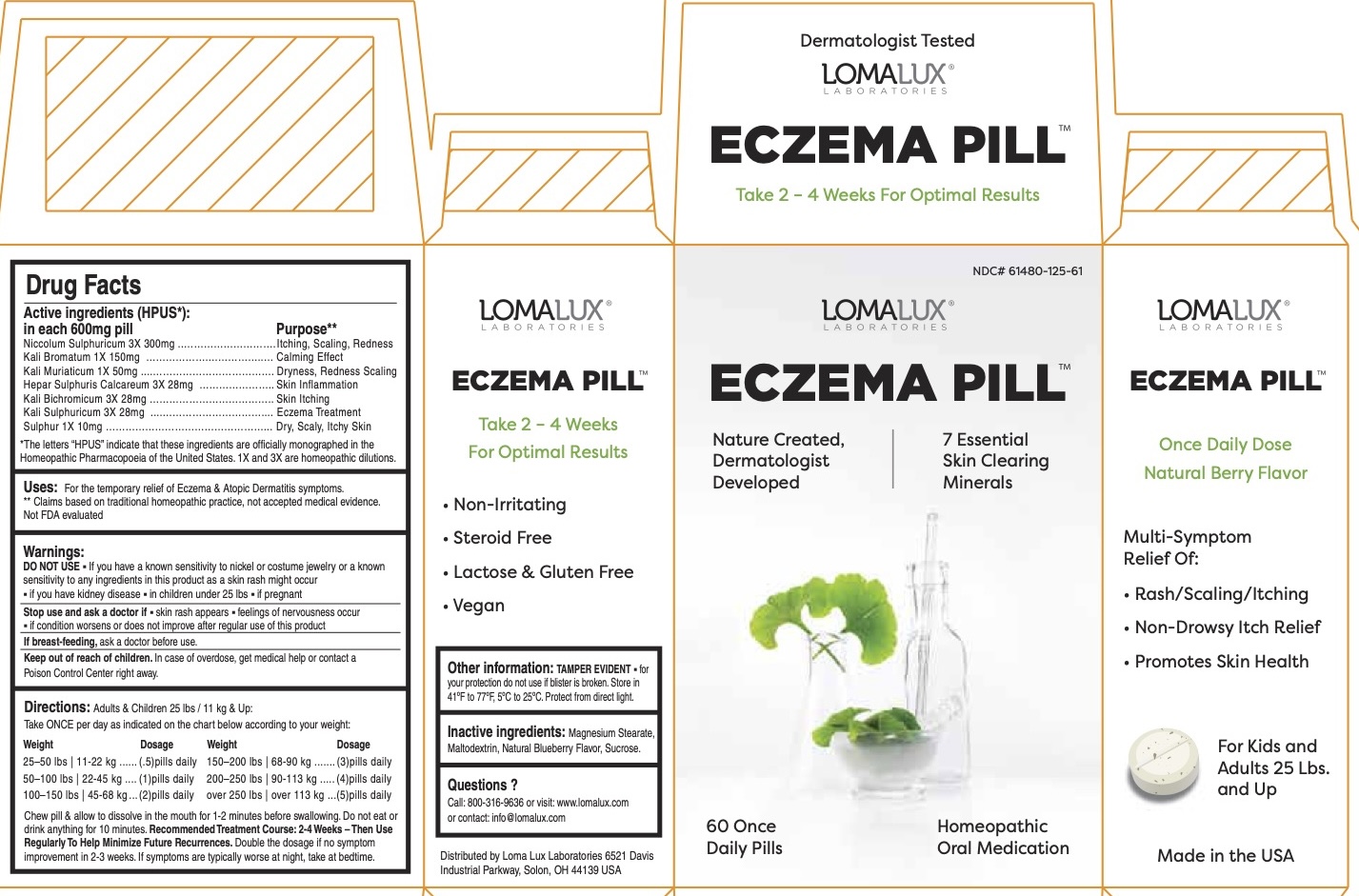 DRUG LABEL: ECZEMA
NDC: 61480-125 | Form: TABLET, CHEWABLE
Manufacturer: PLYMOUTH HEALTHCARE PRODUCTS LLC
Category: homeopathic | Type: HUMAN OTC DRUG LABEL
Date: 20251120

ACTIVE INGREDIENTS: NICKEL SULFATE HEXAHYDRATE 3 [hp_X]/1 1; POTASSIUM BROMIDE 1 [hp_X]/1 1; POTASSIUM CHLORIDE 1 [hp_X]/1 1; CALCIUM SULFIDE 3 [hp_X]/1 1; POTASSIUM DICHROMATE 3 [hp_X]/1 1; POTASSIUM SULFATE 3 [hp_X]/1 1; SULFUR 1 [hp_X]/1 1
INACTIVE INGREDIENTS: MALTODEXTRIN; BLUEBERRY; MAGNESIUM STEARATE; SUCROSE

ECZEMA PILL

Drug Facts
Active ingredients (HPUS*) in each 600mg pill | Purpose**
Niccolum Sulphuricum 3X 300mg | Itching, Scaling, Redness
Kali Bromatum 1X 150mg | Calming Effect
Kali Muriaticum 1X 50mg | Dryness, Redness, Scaling
Hepar Sulphuris Calcareum 3X 28mg | Skin Inflammation
Kali Bichromicum 3X 28mg | Skin Itching
Kali Sulphuricum 3X 28mg | Eczema Treatment
Sulphur 1X 10mg | Dry, Scaly, Itchy Skin

*The letters "HPUS" indicate that these ingredients are officially monographed in the Homeopathic Pharmacopoeia of the United States.

**Claims based on traditional homeopathic practice, not accepted medical evidence. Not FDA evaluated.

INDICATIONS AND USAGE

Uses:For the temporary relief of Eczema & Atopic Dermatitis symptoms.

Warnings:

DO NOT USE

- if you have kidney disease
- in children under 25 lbs
- if pregnant

Ask a doctor before use if

• you have a known sensitivity to nickel or costume jewelry.

• a known sensitivity to any ingredients in this product.

Stop use and ask a doctor if

- skin rash appears
- feelings of nervousness occur
- if condition worsens or does not imporve after regular use of this product.

----------------------------------------------------------------------------------------------------------------------------------------- If pregnant,do not use.

If breast-feeding, ask a doctor before use.

-----------------------------------------------------------------------------------------------------------------------------------------

Keep out of reach of children.In case of overdose, get medical help or contact a Poison Control Center right away.

Keep out of reach of children.

DOSAGE AND ADMINISTRATION

Directions:Adults & Children 25 lbs & Up:

Take ONCE per day as indicated on the chart below according to your weight:

Weight Daily Dosage

25 - 50 lbs ......................... (.5) Pills Daily

50 - 100 lbs ....................... (1) Pills Daily

100 - 150 lbs ..................... (2) Pills Daily

150 - 200 lbs ..................... (3) Pills Daily

Over 200 lbs ...................... (4) Pills Daily

Over 250 lbs.......................(5) Pills Daily

Chew pill & allow to dissolve in the mouth for 1-2 minutes before swallowing. Do not eat or drink anything for 10 minutes after swallowing for maximum effectiveness. Recommended treatment course: 2-4 weeks.Continue using as long as beneficial. Increase dosage by 50% if symptoms do not imporove after 1 week.

Other information

- TAMPER EVIDENT
- for your protection do not use if blister is broken.

INACTIVE INGREDIENT

Inactive ingredients:Magnesium Stearate, Maltodextrin, Natural Blueberry Flavor, Sucrose.

Questions or Comments?

Call 800-316-9636, Monday through Friday, 9am - 5pm EST or visit www.lomalux.com

Distributed by Loma Lux Laboratories: 6521 Davis Industrial Parkway, Solon OH 44139 USA

For Kids & Adults

Dermatologist Developed

LOMALUX

LABORATORIES

ECZEMA PILL

WE TARGET ECZEMA AT ITS SOURCE - WELLNESS FROM WITHIN

As Eczema begins internally why use as a topical band aid? Just like your daily vitamin, Eczema Pill is taken orally to relieve eczema scaling and itching from the inside out for healthy skin from within. With just one daily dose, Eczema Pill's 7 all natural mineral ingredients help relieve all ezcema symptons for kids and adults weighing 25 lbs. & up.

WHEN USED REGULARLY, MAY HELP RELIEVE ECZEMA SYMPTOMS

NATURE CREATED - DERMATOLOGIST PERFECTED.

We use only the finest quality ingredients in our exclusive formulation developed by our dermatologist founder to promote healthy skin from within. A perfect blend of science and nature.

• NON-IRRITATING

• NON-DRYING

• STEROID FREE

• NON DROWSY

Made in USA

NATURAL active ingredients

LACTOSE FREE

VEGAN

GLUTEN FREE

For Kids & Adults

Dermatologist Developed

LOMALUX

LABORATORIES

EXCLUSIVE MINERAL TECHNOLOGY PROMOTES SKIN HEALTH

7 Exclusive Active Mineral ingredients help relive eczema symptoms of scaling, itching & inflammation. These minerals are all natural, earth derived.

FOR ADULTS & KIDS 25 lbs. & UP

Gentle and effective for both kids and big kids alike.

• NON-IRRITATING

• NON-DRYING

• STEROID FREE

• NON DROWSY

No harsh steroids, antihistamines that can cause drowsiness, or other irritating ingredients.

CUSTOMIZED DOSAGE ACCORDING TO YOUR WEIGHT

• FOR OPTIMAL RESULTS

NATURAL

active ingredients

LACTOSE FREE

VEGAN

GLUTEN FREE

PACKAGE LABEL

NDC# 61480-125-61

For Kids & Adults

LOMALUX LABORATORIES

ECZEMA PILL

WELLNESS FROM WITHIN

HEALTHY SKIN FORMULA Nathurally Helps Relieve Itching Inflammation

24 HOUR ONE DOSE Naturally Helps Clear Eczema

Natural Berry Flavor Naturally Helps Prevent Recurrences

Steroid Free

60 QUICK DISSOLVING PILLS

HOMEOPATHIC ORAL MEDICATION

PURPOSE

Naturally Helps Relive

Itching Inflammation

Naturally

Helps Clear Eczema

Naturally Helps

Prevent Recurrences

Steroid Free